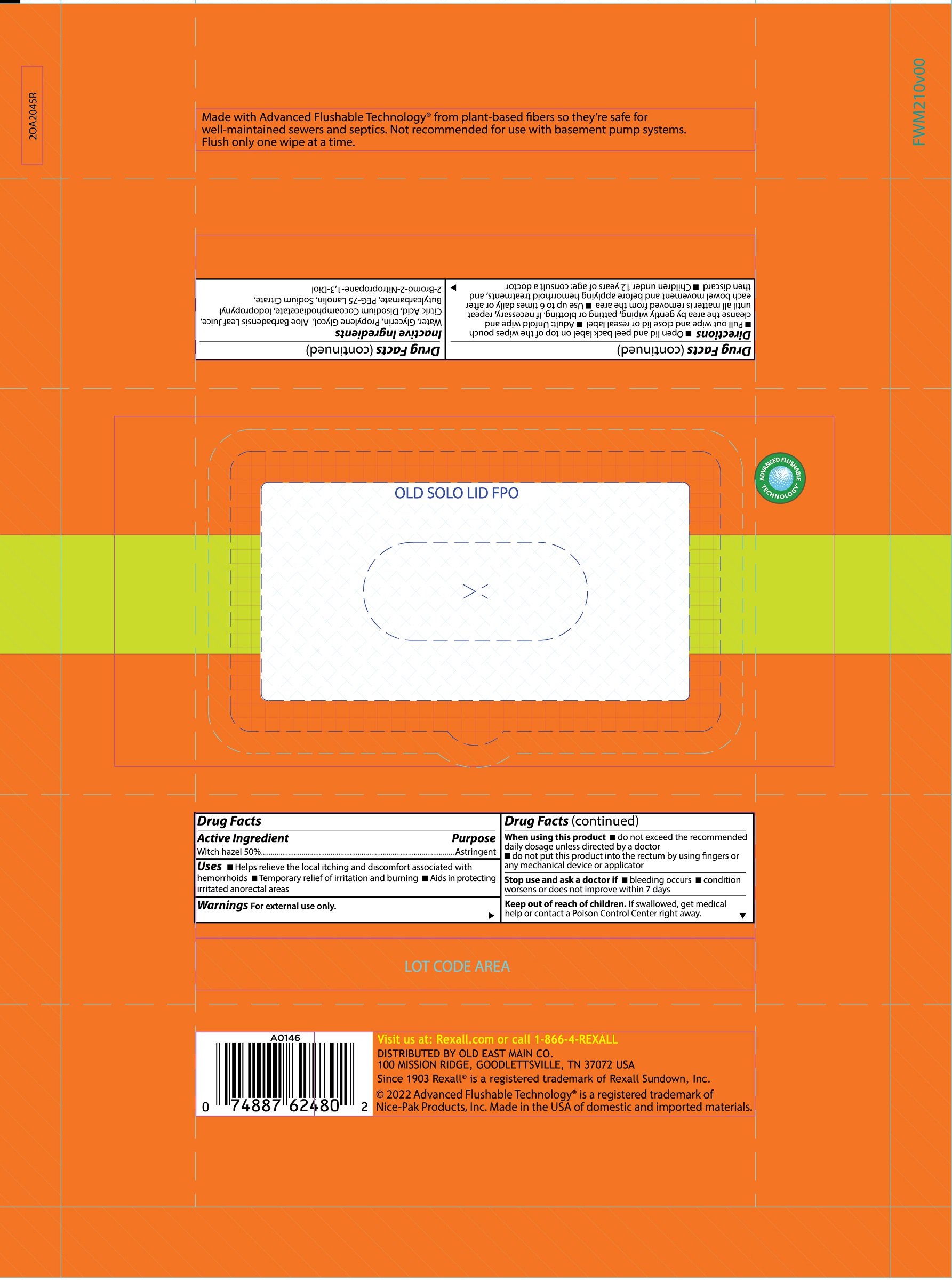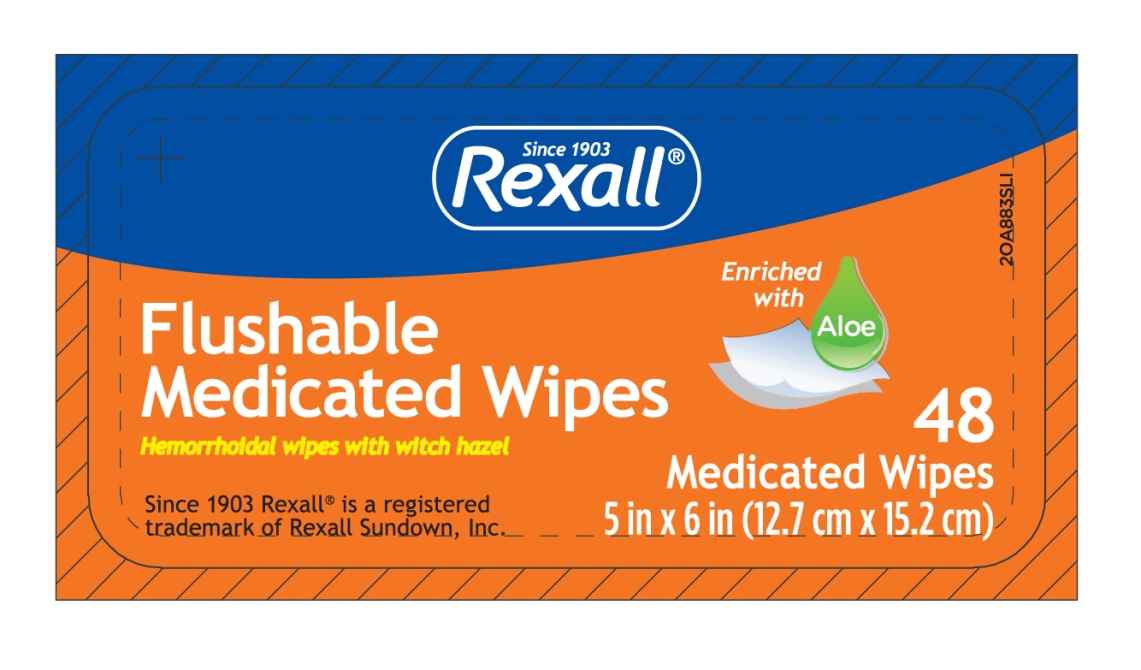 DRUG LABEL: Rexall Medicated WipesHemorrhoidal wipe
NDC: 55910-105 | Form: CLOTH
Manufacturer: Dolgencorp, LLC
Category: otc | Type: HUMAN OTC DRUG LABEL
Date: 20241107

ACTIVE INGREDIENTS: WITCH HAZEL 129 g/258 g
INACTIVE INGREDIENTS: WATER; GLYCERIN; PROPYLENE GLYCOL; ANHYDROUS CITRIC ACID; IODOPROPYNYL BUTYLCARBAMATE; DISODIUM COCOAMPHODIACETATE; BRONOPOL; ALOE ARBORESCENS LEAF; SODIUM CITRATE; PEG-75 LANOLIN

REXALL MEDICATED WIPES

Active Ingredient

Witch hazel 50%

Purpose

Astringent

Uses

- Helps relieve the local itching and discomfort associated with hemorrhoids
- Temporary relief of irritation and burning
- Aids in protecting irritated anorectal areas

Warnings

For external use only

When using this product

- do not exceed the recommended daily dosage unless directed by a doctor
- do not put this product into the rectum by using fingers or any mechanical device or applicator

Stop use and ask a doctor if

- bleeding occurs
- condition worsens or does not improve within 7 days

Keep out of reach of children

If swallowed, get medical help or contact a Poison Control Center right away.

Directions

- Open lid and peel back label on top of the wipes pouch
- Pull out wipe and close lid or reseal label
- Adult: unfold wipe and cleanse the area by gently wiping, patting or blotting. If necessary, repeat until all matter is removed from the area.
- Use up to 6 times daily or after each bowel movement and before applying hemorrhoidal treatments, and then discard
- Children under 12 years of age: consult a doctor

Other information

- store at room temperature 20-25°C (68-77°F)
- for vaginal care - cleanse the area by gently wiping, patting, or blotting. Repeat as needed.
- for use as moist compress - if necessary, first cleanse the area as previously described. Fold wipe to desire size and place in contact with tissue for a soothing and cooling effect. Leave in place for 15 minutes and repeat as needed.

Inactive Ingredients

Water, Glycerin, Propylene Glycol, Aloe Barbadensis Leaf Juice, Ciric Acid, Disodium Cocoamphodiacetate, Iodopropynyl Butylcarbamate, PEG-75 Lanolin, Sodium Citrate, 2-Bomo-2-Nitropropane-1,3-Diol

Unclassified Section

48 Medicated Wipes

5 in. x 6 in. (12.7 cm x 15.2 cm)

Flushable Medicated Wipes

Enriched with Aloe

Hemorrhoidal wipes with witch hazel

Since 1903 Rexall(R) is a registered trademark of Rexall Sundown, Inc.

Made with Advanced Flushable Technology(R) from 100% plant-based materials so they're safe for well-maintained sewers and septics. Not recommended for use with basement pump systems. Flush only one wipe at a time.

Visit us at: Rexall.com

or call 1-866-4-REXALL

PACKAGED FOR DOLGENCORP LLC

100 MISSION RIDGE

GOODLETTSVILLE, TN 37072 USA

(C) 2017 Advanced Flushable Technology(R) is a registered trademark of Nice-Pak Products, Inc. Made in the USA of domestic and imported materials.

Principal Display Panel

lid

flow wrap